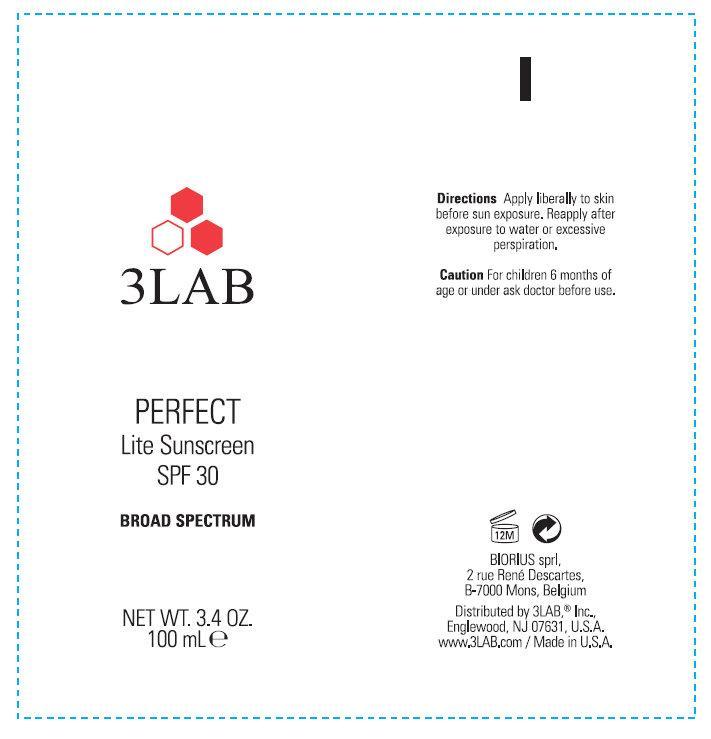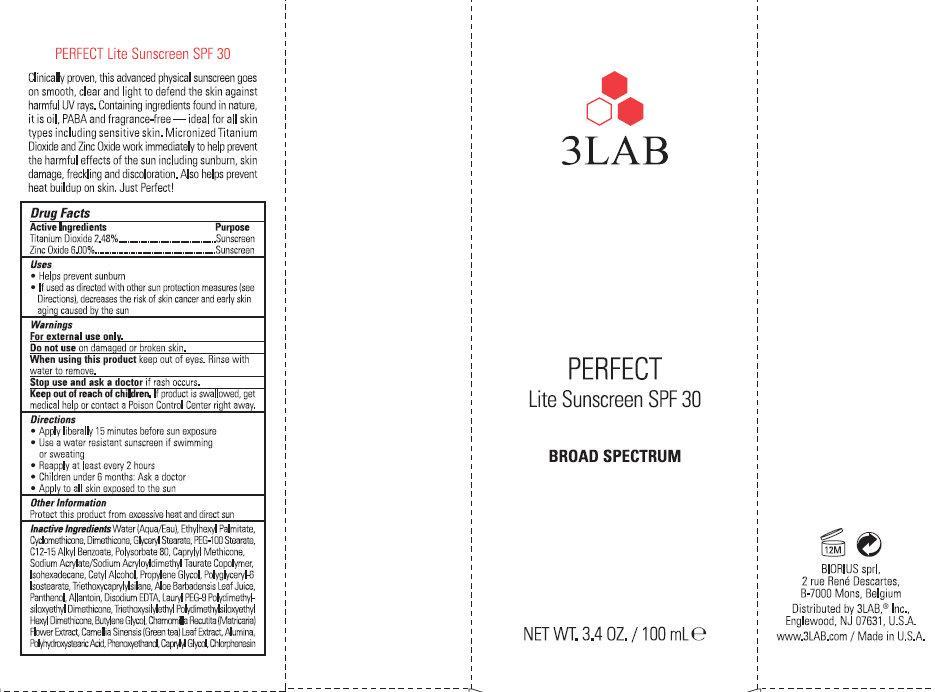 DRUG LABEL: 3LAB PERFECT Lite Sunscreen SPF 30 Broad Spectrum
NDC: 76159-234 | Form: CREAM
Manufacturer: 3LAB, Inc
Category: otc | Type: HUMAN OTC DRUG LABEL
Date: 20231212

ACTIVE INGREDIENTS: TITANIUM DIOXIDE 24.8 mg/1 mL; ZINC OXIDE 60 mg/1 mL
INACTIVE INGREDIENTS: CETYL ALCOHOL; PROPYLENE GLYCOL; TRIETHOXYCAPRYLYLSILANE; ALOE VERA LEAF; PANTHENOL; ALLANTOIN; EDETATE DISODIUM; BUTYLENE GLYCOL; CHAMOMILE; GREEN TEA LEAF; ALUMINUM OXIDE; PHENOXYETHANOL; CAPRYLYL GLYCOL; CHLORPHENESIN; WATER; ETHYLHEXYL PALMITATE; CYCLOMETHICONE; DIMETHICONE; GLYCERYL MONOSTEARATE; PEG-100 STEARATE; ALKYL (C12-15) BENZOATE; POLYSORBATE 80; ISOHEXADECANE

3LAB PERFECT Lite Sunscreen SPF 30 Broad Spectrum

3LAB PERFECT Lite Sunscreen SPF 30 Broad Spectrum

TITANIUM DIOXIDE 2.48% ZINC OXIDE 6.00%

Active Ingredients

TITANIUM DIOXIDE 2.48% ZINC OXIDE 6.00%

Purpose

Sunscreen

Uses

- Helps prevent sunburn
- If used as directed with other sun protection measures (see directions), decreases the risk of skin cancer and early skin aging caused by the sun

Warnings

For external use only.

on damaged or broken skin. Do not use

WHEN USING

keep out of eyes. Rinse with water to remove. When using this product

STOP USE

if rash occurs. Stop use and ask a doctor

Keep out of reach of children.

If product is swallowed, get medical help or contact a Poison Control Center right away.

Directions

- Apply liberally 15 minutes before sun exposure
- Use a water resistant sunscreen if swimming or sweating
- Reapply at least every 2 hours
- Children under 6 months: Ask a doctor
- Apply to all skin exposed to the sun

Other Information

Protect this product from excessive heat and direct sun

Inactive Ingredients

Water (Aqua/Eau), Ethylhexyl Palmitate, Cyclomethicone, Dimethicone, Glyceryl Stearate, PEG-100 Stearate, C12-15 Alkyl Benzoate, Polysorbate 80, Caprylyl Methicone, Sodium Acrylate/Sodium Acryloyldimethyl Taurate Copolymer, Isohexadecane, Cetyl Alcohol, Propylene Glycol, Polyglyceryl-6 Isostearate, Triethoxycaprylylsilane, Aloe Barbadensis Leaf Juice, Panthenol, Allantoin, Disodium EDTA, Lauryl PEG-9 Polydiemthylsiloxyethyl Dimethicone, Triethoxysilylethyl Polydimethylsiloxyethyl Hexyl Dimethicone, Butylene Glycol, Chamomilla Recutita (Matricaria) Flower Extract, Camellia Sinensis (Green Tea) Leaf Extract, Alumina, Polyhydroxystearic Acid, Phenoxyethanol, Caprylyl Glycol, Chlorphenesin.

DESCRIPTION

PERFECT Lite Sunscreen SPF 30 Clinically proven, this advanced physical sunscreen goes on smooth, clean and light to defend the skin against harmful UV rays. Containing ingredients found in nature, it is oil, PABA and fragrance-free - ideal for all skin types including sensitive skin. Micronized Titanium Dioxide and Zinc Oxide work immediately to help prevent the harmful effects of the sun including sunburn, skin damage, freckling and discoloration. Also helps prevent heat buildup on skin. Just Perfect!